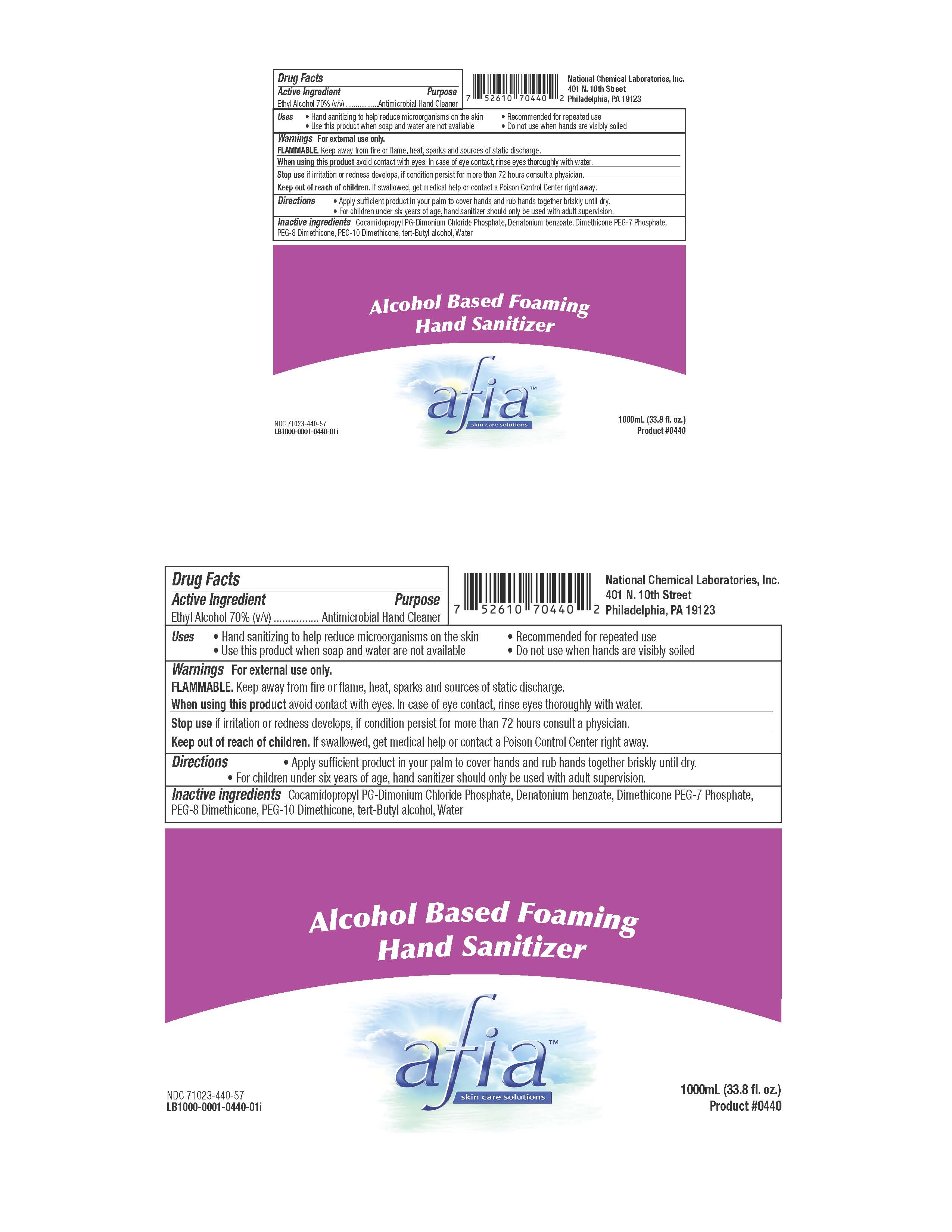 DRUG LABEL: Alcohol Based Foaming Hand Sanitizer
NDC: 71023-440 | Form: LIQUID
Manufacturer: National Chemical Laboratories, Inc.
Category: otc | Type: HUMAN OTC DRUG LABEL
Date: 20221028

ACTIVE INGREDIENTS: ALCOHOL 70 mL/100 mL
INACTIVE INGREDIENTS: PEG-8 DIMETHICONE; TERT-BUTYL ALCOHOL; DIMETHICONE PEG-7 PHOSPHATE; PEG-10 DIMETHICONE (600 CST); COCAMIDOPROPYL PG-DIMONIUM CHLORIDE PHOSPHATE; DENATONIUM BENZOATE; WATER

Alcohol Based Foaming Hand Sanitizer

Active Ingredient(s)

Ethyl Alcohol 70% v/v. Purpose: Antiseptic, Antimicrobial

Alcohol Based Foaming Hand Sanitizer Approval Label

Purpose

Antiseptic, Hand Sanitizer, Antimicrobial

See Image "Alcohol Based Foaming Hand Sanitizer Approval Label"

Use

• Hand sanitizing to help reduce microorganisms on the skin • Recommended for repeated use
• Use this product when soap and water are not available • Do not use when hands are visibly soiled

See "Alcohol Based Foaming Hand Sanitizer FDA Approval Label"

Warnings

For external use only.
FLAMMABLE. Keep away from fire or flame, heat, sparks and sources of static discharge.

See "Alcohol Based Foaming Hand Sanitizer FDA Approval Label"

Do Not Use

- Stop use if irritation or redness develops, if condition persist for more than 72 hours consult a physician.
- See "Alcohol Based Foaming Hand Sanitizer FDA Approval Label"

When using this product avoid contact with eyes. In case of eye contact, rinse eyes thoroughly with water.

Keep out of reach of children. If swallowed, get medical help or contact a Poison Control Center right away.

See "Alcohol Based Foaming Hand Sanitizer FDA Approval Label"

Stop use if irritation or redness develops, if condition persist for more than 72 hours consult a physician.

See "Alcohol Based Foaming Hand Sanitizer FDA Approval Label"

Keep out of reach of children. If swallowed, get medical help or contact a Poison Control Center right away.

See "Alcohol Based Foaming Hand Sanitizer FDA Approval Label"

Directions

- • Apply sufficient product in your palm to cover hands and rub hands together briskly until dry.
  • For children under six years of age, hand sanitizer should only be used with adult supervision.
- See "Alcohol Based Foaming Hand Sanitizer FDA Approval Label"

Other information

- FLAMMABLE. Keep away from fire or flame, heat, sparks and sources of static discharge.
- See "Alcohol Based Foaming Hand Sanitizer FDA Approval Label"

Inactive ingredients

Cocamidopropyl PG-Dimonium Chloride Phosphate, Denatonium benzoate, Dimethicone PEG-7 Phosphate, PEG-8 Dimethicone, PEG-10 Dimethicone, tert-Butyl alcohol, Water

See "Alcohol Based Foaming Hand Sanitizer FDA Approval Label"

Package Label - Principal Display Panel

1000 ml NDC: 71023-440-57

See "Alcohol Based Foaming Hand Sanitizer FDA Approval Label"